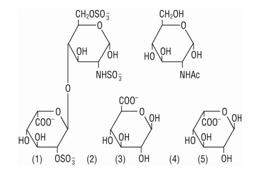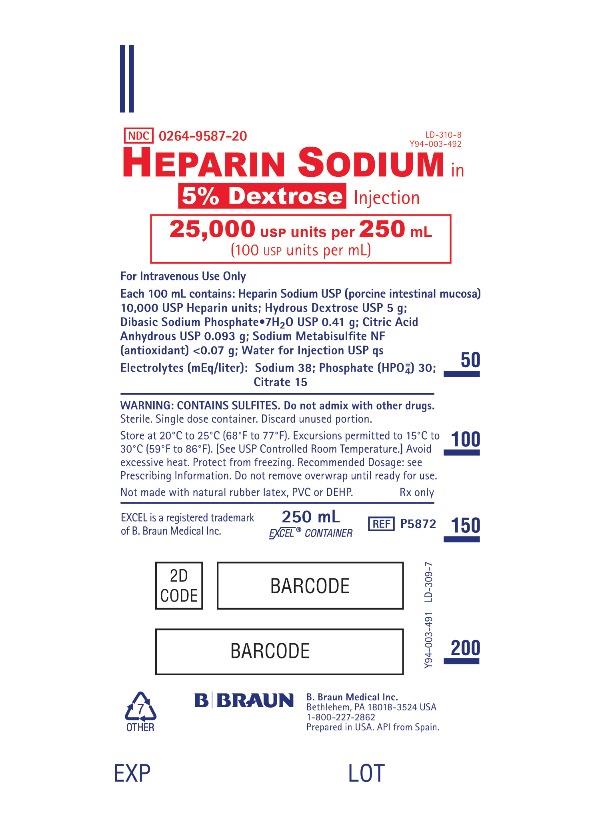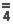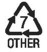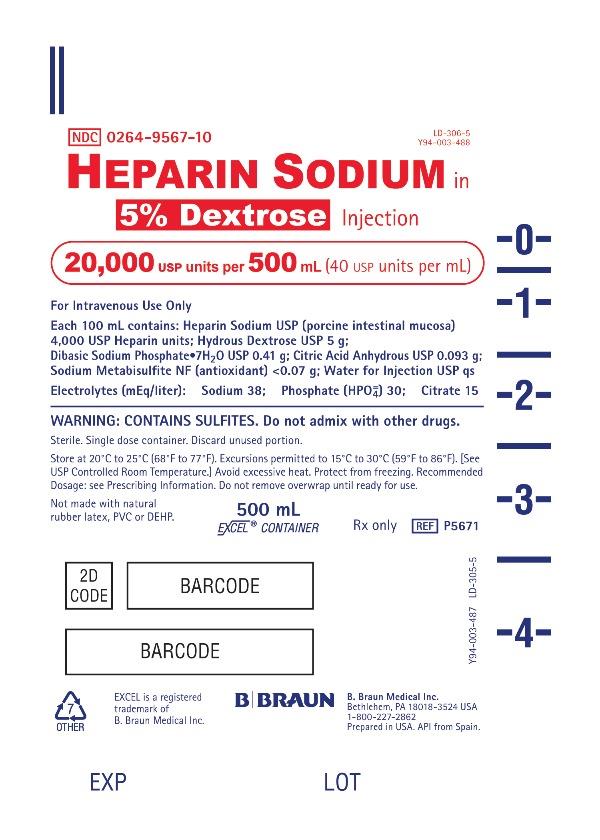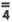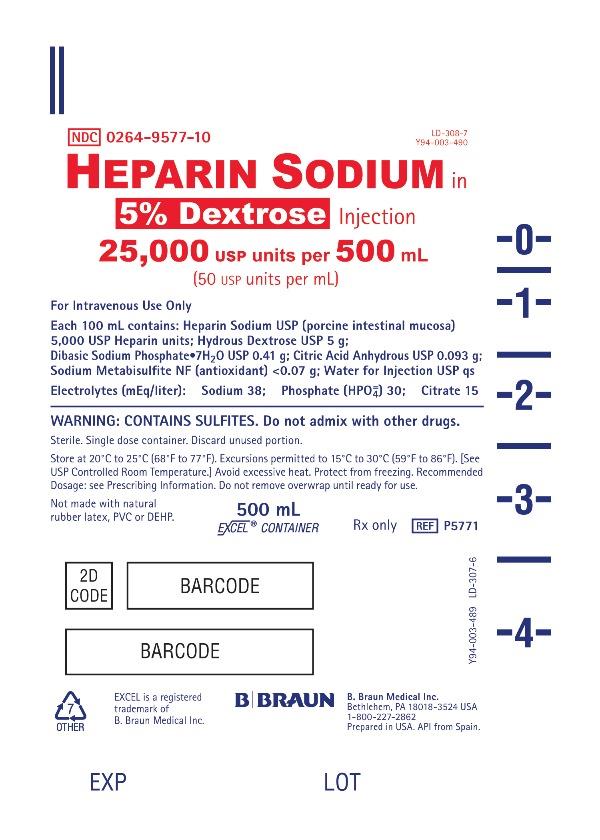 DRUG LABEL: Heparin Sodium in Dextrose
NDC: 0264-9567 | Form: INJECTION
Manufacturer: B. Braun Medical Inc.
Category: prescription | Type: HUMAN PRESCRIPTION DRUG LABEL
Date: 20230731

ACTIVE INGREDIENTS: HEPARIN SODIUM 4000 [USP'U]/100 mL; DEXTROSE MONOHYDRATE 5 g/100 mL
INACTIVE INGREDIENTS: WATER; SODIUM PHOSPHATE, DIBASIC 0.41 g/100 mL; ANHYDROUS CITRIC ACID 0.093 g/100 mL; SODIUM METABISULFITE 0.07 g/100 mL

HIGHLIGHTS OF PRESCRIBING INFORMATION

These highlights do not include all the information needed to use HEPARIN SODIUM IN 5% DEXTROSE INJECTION safely and effectively. See full prescribing information for HEPARIN SODIUM IN 5% DEXTROSE INJECTION.
HEPARIN SODIUM IN 5% DEXTROSE INJECTION, for intravenous use
Initial U.S. Approval: 1939

1 INDICATIONS AND USAGE

Heparin sodium is indicated for: (1)

- Prophylaxis and treatment of venous thrombosis and pulmonary embolism;
- Prophylaxis and treatment of thromboembolic complications associated with atrial fibrillation;
- Treatment of acute and chronic consumption coagulopathies (disseminated intravascular coagulation);
- Prevention of clotting in arterial and cardiac surgery;
- Prophylaxis and treatment of peripheral arterial embolism;
- Anticoagulant use in blood transfusions, extracorporeal circulation, and dialysis procedures.

2 DOSAGE AND ADMINISTRATION

Recommended Adult Dosages:

- Therapeutic Anticoagulant Effect with Full-Dose Heparin* (2.3)

Intermittent Intravenous Injection | Initial Dose | 10,000 Units
Intermittent Intravenous Injection | Subsequent Doses | 5,000 to 10,000 Units every 4 to 6 hours
Continuous Intravenous Infusion | Initial Dose | 5,000 Units by intravenous injection
Continuous Intravenous Infusion | Continuous | 20,000 to 40,000 Units every 24 hours

* Based on 150 lb. (68 kg) patient.

- Cardiovascular Surgery (2.5)

Intravascular via Total Body Perfusion | Initial Dose | Greater than or equal to 150 units/kg; adjust for longer procedures

- Extracorporeal Dialysis (2.8)

Intravascular via Extracorporeal Dialysis | Follow equipment manufacturer's operating directions carefully.

For pediatric dosing see section 2.4 of full prescribing information.

3 DOSAGE FORMS AND STRENGTHS

- Heparin Sodium 20,000 USP units per 500 mL (40 USP units per mL) in 5% Dextrose Injection (3)
- Heparin Sodium 25,000 USP units per 500 mL (50 USP units per mL) in 5% Dextrose Injection (3)
- Heparin Sodium 25,000 USP units per 250 mL (100 USP units per mL) in 5% Dextrose Injection (3)

4 CONTRAINDICATIONS

- History of heparin-induced thrombocytopenia (HIT) or heparin-induced thrombocytopenia and thrombosis (HITT) (5.3)
- Known hypersensitivity to heparin or pork products (5.7)
- In whom suitable blood coagulation tests cannot be performed at appropriate intervals (5.5)
- Uncontrollable active bleeding state, except when this is due to disseminated intravascular coagulation (5.2)

5 WARNINGS AND PRECAUTIONS

- Fatal Medication Errors: Confirm choice of correct strength prior to administration. (5.1)
- Hemorrhage: Fatal cases have occurred. Monitor for signs of bleeding and manage promptly. (5.2)
- HIT or HITT: Monitor for signs and symptoms and discontinue if indicative of HIT or HITT. (5.3)
- Thrombocytopenia: Monitor platelet count during therapy; discontinue heparin in HIT or HITT is suspected. (5.4)
- Monitoring: Blood coagulation tests guide therapy for full-dose heparin. Monitor platelet count and hematocrit in all patients receiving heparin. (5.5)
- Heparin Resistance: Increased resistance to heparin is frequently encountered in fever, thrombosis, thrombophlebitis, infections with thrombosing tendencies, myocardial infarction, cancer and in postsurgical patients. (5.6)
- Hypersensitivity Reactions: Use in patients with prior reactions only in life-threatening situations. (5.7)
- Hyperkalemia: Measure plasma potassium in patients at risk of hyperkalemia before starting heparin therapy and periodically in all patients (5.8)
- Elevations of serum aminotransferases: Interpret elevation of these enzymes with caution. (5.9)

6 ADVERSE REACTIONS

Most common adverse reactions are: hemorrhage, thrombocytopenia, HIT or HITT, heparin resistance, hypersensitivity reactions, hyperkalemia, and elevations of aminotransferase levels. (6)

To report SUSPECTED ADVERSE REACTIONS, contact B. Braun Medical Inc. at 1-800-227-2862 or FDA at

1-800-FDA-1088 or www.fda.gov/medwatch.

7 DRUG INTERACTIONS

- Drugs that interfere with coagulation, platelet aggregation or drugs that counteract coagulation may induce bleeding. (7)

FULL PRESCRIBING INFORMATION

1 INDICATIONS AND USAGE

Heparin Sodium in 5% Dextrose Injection is indicated for:

- Prophylaxis and treatment of venous thrombosis and pulmonary embolism
- Prophylaxis and treatment of thromboembolic complications associated with atrial fibrillation
- Treatment of acute and chronic consumption coagulopathies (disseminated intravascular coagulation)
- Prevention of clotting in arterial and cardiac surgery
- Prophylaxis and treatment of peripheral arterial embolism
- Anticoagulant use in blood transfusions, extracorporeal circulation, and dialysis procedures.

2 DOSAGE AND ADMINISTRATION

2.1 Preparation for Administration

Confirm the selection of the correct formulation and strength prior to administration of the drug.

This product should be administered by intravenous infusion.

Do not use Heparin Sodium in 5% Dextrose Injection as a “catheter lock flush” product.

Do not admix with other drugs.

Discard unused portion.

Do not use plastic containers in series connection.

This product should not be infused under pressure.

Parenteral drug products should be inspected visually for particulate matter and discoloration prior to administration, whenever solution and container permit. Use only if solution is clear and container and seals are intact.

2.2 Laboratory Monitoring for Efficacy and Safety

Adjust the dosage of heparin sodium according to the patient’s coagulation test results. When heparin is given by continuous intravenous infusion, determine the coagulation time approximately every 4 hours in the early stages of treatment. When the drug is administered intermittently by intravenous injection, perform coagulation tests before each injection during the early stages of treatment and at appropriate intervals thereafter. Dosage is considered adequate when the activated partial thromboplastin time (APTT) is 1.5 to 2 times the normal or when the whole blood clotting time is elevated approximately 2.5 to 3 times the control value.

Periodic platelet counts, hematocrits, and tests for occult blood in stool are recommended during the entire course of heparin therapy.

2.3 Therapeutic Anticoagulant Effect with Full-Dose Heparin

The dosing recommendations in Table 1 are based on clinical experience. Although dosage must be adjusted for the individual patient according to the results of suitable laboratory tests, the following dosage schedules may be used as guidelines:

Table 1: Recommended Adult Full-Dose Heparin Regimens for Therapeutic Anticoagulant Effect

Method of Administration | Frequency | Recommended Dose [Based on 150 lb. (68 kg) patient.]
Intermittent Intravenous Injection | Initial Dose | 10,000 Units
Intermittent Intravenous Injection | Subsequent Doses | 5,000 to 10,000 Units every 4 to 6 hours
Continuous Intravenous Infusion | Initial Dose | 5,000 Units by intravenous injection
Continuous Intravenous Infusion | Continuous | 20,000 to 40,000 Units every 24 hours

2.4 Pediatric Use

There are no adequate and well-controlled studies on heparin use in pediatric patients. Pediatric dosing recommendations are based on clinical experience. In general, the following dosage schedule may be used as a guideline in pediatric patients:

Initial Dose | 75 units/kg to 100 units/kg (intravenous bolus over 10 minutes)
Maintenance Dose | Infants: 25 units/kg/hour to 30 units/kg/hour;; Infants < 2 months have the highest requirements (average 28 units/kg/hour); Children > 1 year of age: 18 units/kg/hour to 20 units/kg/hour;; Older children may require less heparin, similar to weight-adjusted adult dosage
Monitoring | Adjust heparin to maintain APTT of 60 to 85 seconds, assuming this reflects an anti-Factor Xa level of 0.35 to 0.70.

2.5 Cardiovascular Surgery

Patients undergoing total body perfusion for open-heart surgery should receive an initial dose of not less than 150 units of heparin sodium per kilogram of body weight. Frequently, a dose of 300 units per kilogram is used for procedures estimated to last less than 60 minutes or 400 units per kilogram for those estimated to last longer than 60 minutes.

2.6 Converting to Warfarin

To ensure continuous anticoagulation when converting from HEPARIN SODIUM to warfarin, continue full heparin therapy for several days until the INR (prothrombin time) has reached a stable therapeutic range. Heparin therapy may then be discontinued without tapering [see Drug Interactions (7.1)].

2.7 Converting to Oral Anticoagulants other than Warfarin

For patients currently receiving intravenous heparin, stop intravenous infusion of heparin sodium immediately after administering the first dose of oral anticoagulant; or for intermittent intravenous administration of heparin sodium, start oral anticoagulant 0 to 2 hours before the time that the next dose of heparin was to have been administered.

2.8 Extracorporeal Dialysis

Follow equipment manufacturer’s operating directions carefully. A dose of 25 to 30 units/kg followed by an infusion rate of 1,500 to 2,000 units/hour is suggested based on pharmacodynamic data if specific manufacturers’ recommendations are not available.

3 DOSAGE FORMS AND STRENGTHS

HEPARIN SODIUM IN 5% DEXTROSE INJECTION is available as:

• Heparin Sodium 20,000 USP units per 500 mL (40 USP units per mL) in 5% Dextrose Injection.

• Heparin Sodium 25,000 USP units per 500 mL (50 USP units per mL) in 5% Dextrose Injection.

• Heparin Sodium 25,000 USP units per 250 mL (100 USP units per mL) in 5% Dextrose Injection.

4 CONTRAINDICATIONS

The use of HEPARIN SODIUM in 5% Dextrose Injection is contraindicated in patients with the following conditions:

- History of heparin-induced thrombocytopenia (HIT) and heparin-induced thrombocytopenia and thrombosis (HITT) [see Warnings and Precautions (5.3)]
- Known hypersensitivity to heparin or pork products (e.g., anaphylactoid reactions) [see Warnings and Precautions (5.7) and Adverse Reactions (6.1)]
- In whom suitable blood coagulation tests – e.g., the whole blood clotting time, partial thromboplastin time, etc., – cannot be performed at appropriate intervals (this contraindication refers to full-dose heparin; there is usually no need to monitor coagulation parameters in patients receiving low-dose heparin) [see Warnings and Precautions (5.5)]
- Uncontrollable active bleeding state except when this is due to disseminated intravascular coagulation [see Warnings and Precautions (5.2)]

5 WARNINGS AND PRECAUTIONS

5.1 Fatal Medication Errors

Do not use this product as a “catheter lock flush” product. Heparin is supplied in various strengths. Fatal hemorrhages have occurred due to medication errors. Carefully examine all heparin products to confirm the correct container choice prior to administration of the drug.

5.2 Hemorrhage

Hemorrhage, including fatal events, has occurred in patients receiving HEPARIN SODIUM. Avoid using heparin in the presence of major bleeding, except when the benefits of heparin therapy outweigh the potential risks.

Hemorrhage can occur at virtually any site in patients receiving heparin. Adrenal hemorrhage (with resultant acute adrenal insufficiency), ovarian hemorrhage, and retroperitoneal hemorrhage have occurred during anticoagulant therapy with heparin [see Adverse Reactions (6.1)]. A higher incidence of bleeding has been reported in patients, particularly women, over 60 years of age [see Clinical Pharmacology (12.3)]. An unexplained fall in hematocrit or fall in blood pressure should lead to serious consideration of a hemorrhagic event.

Use heparin sodium with caution in disease states in which there is increased risk of hemorrhage, including:

- Cardiovascular – Subacute bacterial endocarditis. Severe hypertension.
- Surgical – During and immediately following (a) spinal tap or spinal anesthesia or (b) major surgery, especially involving the brain, spinal cord or eye.
- Hematologic – Conditions associated with increased bleeding tendencies, such as hemophilia, thrombocytopenia and some vascular purpuras.
- Patients with hereditary antithrombin III deficiency receiving concurrent antithrombin III therapy – The anticoagulant effect of heparin is enhanced by concurrent treatment with antithrombin III (human) in patients with hereditary antithrombin III deficiency. To reduce the risk of bleeding, reduce the heparin dose during concomitant treatment with antithrombin III (human).
- Gastrointestinal – Ulcerative lesions and continuous tube drainage of the stomach or small intestine.
- Other – Menstruation, liver disease with impaired hemostasis.

5.3 Heparin-Induced Thrombocytopenia (HIT) and Heparin-Induced Thrombocytopenia and Thrombosis (HITT)

HIT is a serious immune-mediated reaction resulting from irreversible aggregation of platelets. HIT occurs in patients treated with heparin and is due to the development of antibodies to a platelet Factor 4-heparin complex that induce in vivo platelet aggregation. HIT may progress to the development of venous and arterial thromboses, a condition known as HITT. Thrombotic events may also be the initial presentation for HIT. These serious thromboembolic events include deep vein thrombosis, pulmonary embolism, cerebral vein thrombosis, limb ischemia, stroke, myocardial infarction, thrombus formation on a prosthetic cardiac valve, mesenteric thrombosis, renal arterial thrombosis, skin necrosis, gangrene of the extremities that may lead to amputation, and possibly death.

Once HIT or HITT is diagnosed or strongly suspected, discontinue all heparin sources (including heparin flushes) and use an alternative anticoagulant.

Immune-mediated HIT is diagnosed based on clinical findings supplemented by laboratory tests confirming the presence of antibodies to heparin, or platelet activation induced by heparin. Obtain platelet counts at baseline and periodically during heparin administration. A drop in platelet count greater than 50% from baseline is considered indicative of HIT. Platelet counts begin to fall 5 to 10 days after exposure to heparin in heparin–naive individuals and reach a threshold by days 7 to 14. In contrast, “rapid onset” HIT can occur very quickly (within 24 hours following heparin initiation), especially in patients with a recent exposure to heparin (i.e., previous 3 months).

Thrombosis development shortly after documenting thrombocytopenia is a characteristic finding in almost half of all patients with HIT.

Monitor thrombocytopenia of any degree closely. If the platelet count falls below 100,000/mm^3 or if recurrent thrombosis develops, promptly discontinue heparin, evaluate for HIT and HITT, and, if necessary, administer an alternative anticoagulant.

HIT or HITT can occur up to several weeks after the discontinuation of heparin therapy. Patients presenting with thrombocytopenia or thrombosis after discontinuation of heparin should be evaluated for HIT or HITT.

5.4 Thrombocytopenia

Thrombocytopenia has been reported to occur in patients receiving heparin with a reported incidence of up to 30%. It can occur 2 to 20 days (average 5 to 9) following the onset of heparin therapy. Obtain platelet counts before and periodically during heparin therapy. Monitor thrombocytopenia of any degree closely. If the count falls below 100,000/mm^3 or if recurrent thrombosis develops, promptly discontinue heparin, evaluate for HIT, and, if necessary, administer an alternative anticoagulant [see Warnings and Precautions (5.3)].

5.5 Coagulation Testing and Monitoring

When using a full dose heparin regimen, adjust the heparin dose based on frequent blood coagulation tests. If the coagulation test is unduly prolonged or if hemorrhage occurs, heparin sodium should be discontinued promptly [see Overdosage (10)]. Periodic platelet counts, hematocrits are recommended during the entire course of heparin therapy [see Dosage and Administration (2.2)].

5.6 Heparin Resistance

Increased resistance to heparin is frequently encountered in fever, thrombosis, thrombophlebitis, infections with thrombosing tendencies, myocardial infarction, cancer and in postsurgical patients, and patients with antithrombin III deficiency.

Consider measurement of anti-thrombin levels if heparin resistance is suspected. Monitor coagulation tests frequently in such patients. It may be necessary to adjust the dose of heparin based on coagulation test monitoring, such as anti-Factor Xa levels and/or partial thromboplastin time.

5.7 Hypersensitivity Reactions

Hypersensitivity reactions with chills, fever and urticaria as the most usual manifestations and also asthma, rhinitis, lacrimation, and anaphylactoid reactions have been reported. Patients with documented hypersensitivity to heparin should be given the drug only in clearly life-threatening situations [see Adverse Reactions (6.1)].

Because Heparin Sodium in 5% Dextrose Injection is derived from animal tissue, monitor for signs and symptoms of hypersensitivity when it is used in patients with a history of allergy to pork products.

This product contains sodium metabisulfite, a sulfite that may cause allergic-type reactions including anaphylactic symptoms and life-threatening or less severe asthmatic episodes in certain susceptible people. The overall prevalence of sulfite sensitivity in the general population is unknown and probably low. Sulfite sensitivity is seen more frequently in asthmatic than in nonasthmatic people.

5.8 Hyperkalemia

Heparin can suppress adrenal secretion of aldosterone leading to hyperkalemia, particularly in patients with diabetes mellitus, chronic renal failure, pre-existing metabolic acidosis, a raised plasma potassium, or taking potassium sparing drugs. The risk of hyperkalemia appears to increase with duration of therapy but is usually reversible upon discontinuation of heparin.

Measure plasma potassium in patients at risk of hyperkalemia before starting heparin therapy and periodically in all patients treated for more than 5 days or earlier as deemed fit by the clinician.

5.9 Elevations of Serum Aminotransferases

Significant elevations of aspartate aminotransferase (AST) and alanine aminotransferase (ALT) levels have occurred in patients who have received heparin. Elevation of these enzymes in patients receiving heparin should be interpreted with caution. These elevations typically resolve upon heparin discontinuation.

6 ADVERSE REACTIONS

The following serious adverse reactions are described elsewhere in the labeling:

- Hemorrhage [see Warnings and Precautions (5.2)]
- Heparin-Induced Thrombocytopenia and Heparin-Induced Thrombocytopenia with Thrombosis [see Warnings and Precautions (5.3)]
- Thrombocytopenia [see Warnings and Precautions (5.4)]
- Heparin Resistance [see Warnings and Precautions (5.6)]
- Hypersensitivity [see Warnings and Precautions (5.7)]
- Hyperkalemia [see Warnings and Precautions (5.8)]
- Elevations of Serum Aminotransferases [see Warnings and Precautions (5.9)]

6.1 Postmarketing Experience

The following adverse reactions have been identified during post-approval use of heparin sodium. Because these reactions are reported voluntarily from a population of uncertain size, it is not always possible to reliably estimate their frequency.

- Hemorrhage – Hemorrhage is the chief complication that may result from heparin therapy [see Warnings and Precautions (5.2)]. An overly prolonged clotting time or minor bleeding during therapy can usually be controlled by withdrawing the drug [see Overdosage (10)]. Gastrointestinal or urinary tract bleeding during anticoagulant therapy may indicate the presence of an underlying occult lesion. Bleeding can occur at any site but certain specific hemorrhagic complications may be difficult to detect:
  - Adrenal hemorrhage, with resultant acute adrenal insufficiency, has occurred with heparin therapy, including fatal cases.
  - Ovarian (corpus luteum) hemorrhage developed in a number of women of reproductive age receiving short- or long-term anticoagulant therapy.
  - Retroperitoneal hemorrhage.

- Vascular Disorders – Contusion, Vasospastic reactions (including episodes of painful, ischemic, and cyanosed limbs).
- HIT and HITT, including delayed onset cases, and Thrombocytopenia – [see Warnings and Precautions (5.3 and 5.4)]
- Histamine-like reactions – Such reactions have been observed at the site of injections. Necrosis of the skin has been reported at the site of subcutaneous injection of heparin, occasionally requiring skin grafting.
- Hypersensitivity – Generalized hypersensitivity reactions have been reported with chills, fever, and urticaria as the most usual manifestations, and asthma, rhinitis, lacrimation, headache, nausea and vomiting, and anaphylactoid reactions, including shock, occurring more rarely. Itching and burning, especially on the plantar site of the feet, may occur [see Warnings and Precautions (5.7)].
- Musculoskeletal, Connective Tissue and Bone Disorders – Osteoporosis with long-term administration of heparin.
- Metabolism and Nutrition Disorders – Hyperkalemia.
- General Disorders and Administration Site Conditions – Erythema, mild pain, ulceration.
- Elevations of serum aminotransferases – Significant elevations of aspartate aminotransferase (AST) and alanine aminotransferase (ALT) levels have occurred in patients who have received heparin.
- Others – Osteoporosis following long-term administration of high-doses of heparin, cutaneous necrosis after systemic administration, suppression of aldosterone synthesis, delayed transient alopecia, priapism, and rebound hyperlipemia on discontinuation of heparin sodium have also been reported.

7 DRUG INTERACTIONS

7.1 Oral Anticoagulants

Heparin sodium may prolong the one-stage prothrombin time. Therefore, when heparin sodium is given with dicumarol or warfarin sodium, a period of at least 5 hours after the last intravenous dose or 24 hours after the last subcutaneous dose should elapse before blood is drawn if a valid prothrombin time is to be obtained.

7.2 Platelet Inhibitors

Drugs such as NSAIDS (including acetylsalicylic acid, ibuprofen, indomethacin, and celecoxib), dextran, phenylbutazone, thienopyridines, dipyridamole, hydroxychloroquine, glycoprotein IIv/IIa antagonists (including abciximab, eptifibatide, and tirofiban), and others that interfere with platelet-aggregation reactions (the main hemostatic defense of heparinized patients) may induce bleeding and should be used with caution in patients receiving heparin sodium. To reduce the risk of bleeding, a reduction in the dose of antiplatelet agent or heparin is recommended.

7.3 Other Medications that May Interfere with Heparin

Digitalis, tetracyclines, nicotine, antihistamines, or intravenous nitroglycerin may partially counteract the anticoagulant action of heparin sodium. Intravenous nitroglycerin administered to heparinized patients may result in a decrease of the partial thromboplastin time with subsequent rebound effect upon discontinuation of nitroglycerin. Careful monitoring of partial thromboplastin time and adjustment of heparin dosage are recommended during coadministration of heparin and intravenous nitroglycerin. Antithrombin III (human) – The anticoagulant effect of heparin is enhanced by concurrent treatment with antithrombin III (human) in patients with hereditary antithrombin III deficiency. To reduce the risk of bleeding, a reduced dosage of heparin is recommended during treatment with antithrombin III (human).

8 USE IN SPECIFIC POPULATIONS

8.1 Pregnancy

Risk Summary

In published reports, heparin exposure during pregnancy did not show evidence of an increased risk of adverse maternal or fetal outcomes in humans. No teratogenicity was observed in animal reproduction studies with administration of heparin sodium to pregnant rats and rabbits during organogenesis at doses up to 10,000 USP units/kg/day, approximately 10 times the maximum recommended human dose (MRHD) of 40,000 USP units/24 hours infusion [see Data]. In pregnant animals, doses up to 10 times higher than the maximum human daily dose based on body weight resulted in increased resorptions. Consider the benefits and risks of HEPARIN SODIUM IN 5% DEXTROSE INJECTION to a pregnant woman and possible risks to the fetus when prescribing HEPARIN SODIUM IN 5% DEXTROSE INJECTION.

The estimated background risk of major birth defects and miscarriage for the indicated population is unknown. In the U.S. general population, the estimated background risk of major birth defects and miscarriage in clinically recognized pregnancies is 2-4% and 15-20%, respectively.

Data

Human Data

The maternal and fetal outcomes associated with uses of heparin via various dosing methods and administration routes during pregnancy have been investigated in numerous studies. These studies generally reported normal deliveries with no maternal or fetal bleeding and no other complications.

Animal Data

In a published study conducted in rats and rabbits, pregnant animals received heparin intravenously during organogenesis at a dose of 10,000 USP units/kg/day, approximately 10 times the maximum human daily dose based on body weight. The number of early resorptions increased in both species. There was no evidence of teratogenic effects.

8.2 Lactation

Risk Summary

There is no information regarding the presence of HEPARIN SODIUM IN 5% DEXTROSE INJECTION in human milk, the effects on the breastfed infant, or the effects on milk production. Due to its large molecular weight, heparin is not likely to be excreted in human milk, and any heparin in milk would not be orally absorbed by a nursing infant. The developmental and health benefits of breastfeeding should be considered along with the mother’s clinical need for HEPARIN SODIUM IN 5% DEXTROSE INJECTION and any potential adverse effects on the breastfed infant from HEPARIN SODIUM IN 5% DEXTROSE INJECTION or from the underlying maternal condition [see Use in Specific Populations (8.4)].

8.4 Pediatric Use

There are no adequate and well controlled studies on heparin use in pediatric patients. Pediatric dosing recommendations are based on clinical experience [see Dosage and Administration (2.4)].

8.5 Geriatric Use

There are limited adequate and well-controlled studies in patients 65 years and older. However, a higher incidence of bleeding has been reported in patients over 60 years of age, especially women [see Warnings and Precautions (5.2)]. Lower doses of heparin may be indicated in these patients [see Clinical Pharmacology (12.3)].

10 OVERDOSAGE

An overdose requires immediate medical attention and treatment.

Symptoms

Bleeding is the chief sign of heparin overdosage. Easy bruising, petechial formations, nosebleeds, blood in urine or tarry stools may be the first signs or symptoms of a heparin overdose. In the event of symptomatic heparin overdose, consider stopping heparin infusion.

Treatment

Neutralization of heparin effect:

When clinical circumstances (bleeding) require reversal of heparinization, protamine sulfate (1% solution) by slow infusion will neutralize heparin sodium. No more than 50 mg should be administered, very slowly, in any 10 minute period. Each mg of protamine sulfate neutralizes approximately 100 USP Heparin units. The amount of protamine required decreases over time as heparin is metabolized. Although the metabolism of heparin is complex, it may, for the purpose of choosing a protamine dose, be assumed to have a half-life of about 30 minutes after intravenous injection.

Ideally, the dose required to neutralize the action of heparin should be guided by blood coagulation tests or calculated from a protamine neutralization test.

Because fatal reactions often resembling anaphylaxis have been reported, protamine sulfate should be given only when resuscitation techniques and treatment of anaphylactoid shock are readily available.

For additional information, consult the prescribing information for Protamine Sulfate Injection, USP.

Blood or plasma transfusions may be necessary; these dilute but do not neutralize heparin.

11 DESCRIPTION

Heparin is a heterogenous group of straight-chain anionic mucopolysaccharides, called glycosaminoglycans having anticoagulant properties. It is composed of polymers of alternating derivations of alpha-L-iduronic acid 2-sulfate (1), 2-deoxy-2-sulfamino- alpha-D-glucose 6-sulfate (2), beta-D-glucuronic acid (3), 2-acetamido-2- deoxy-alpha-D-glucose (4), and alpha-L-iduronic acid (5).

Structure of Heparin Sodium (representative subunits):

Heparin Sodium in 5% Dextrose Injection is a sterile, nonpyrogenic solution prepared from Heparin Sodium USP (derived from porcine intestinal mucosa and standardized for use as an anticoagulant) and Hydrous Dextrose USP. It is to be administered by intravenous injection. The potency is determined by a biological assay using a USP reference standard based on units of heparin activity per milligram.

The pH range is 5.6 (4.5 – 7.0) and the osmolarity mOsmol/L (calc.) is 315. The concentration of electrolytes is 38 mEq/L Sodium, 30 mEq/L Phosphate, and 15 mEq/L Citrate.

40 USP units/mL: Each 100 mL of the 20,000 USP units per 500 mL preparation contains: 4,000 USP units of heparin sodium, 5 g Hydrous Dextrose USP, 0.41 g Dibasic Sodium Phosphate, 0.093 g Citric Acid Anhydrous USP, 0.0686 g Sodium Metabisulfite NF (antioxidant), and Water for Injection USP until quantity sufficient.

50 USP units/mL: Each 100 mL of the 25,000 USP units per 500 mL preparation contains: 5,000 USP units of heparin sodium, 5 g Hydrous Dextrose USP, 0.41 g Dibasic Sodium Phosphate, 0.093 g Citric Acid Anhydrous USP, 0.0686 g Sodium Metabisulfite NF (antioxidant), and Water for Injection USP until quantity sufficient.

100 USP units/mL: Each 100 mL of the 25,000 USP units per 250 mL preparation contains: 10,000 USP units of heparin sodium, 5 g Hydrous Dextrose USP, 0.41 g Dibasic Sodium Phosphate, 0.093 g Citric Acid Anhydrous USP, 0.0686 g Sodium Metabisulfite NF (antioxidant), and Water for Injection USP until quantity sufficient.

The plastic container is made from a multilayered film specifically developed for parenteral drugs. It contains no plasticizers and exhibits virtually no leachables. The solution contact layer is a rubberized copolymer of ethylene and propylene. The container is nontoxic and biologically inert. The container-solution unit is a closed system and is not dependent upon entry of external air during administration. The container is overwrapped to provide protection from the physical environment and to provide an additional moisture barrier when necessary.

The plastic container is not made with natural rubber latex, PVC or DEHP.

The closure system has two ports; the one for the administration set has a tamper evident plastic protector.

12 CLINICAL PHARMACOLOGY

12.1 Mechanism of Action

Heparin interacts with the naturally occurring plasma protein, Antithrombin III, to induce a conformational change, which markedly enhances the serine protease activity of Antithrombin III, thereby inhibiting the activated coagulation factors involved in the closing sequence, particularly Xa and IIa. Small amounts of heparin inhibit Factor Xa, and larger amounts inhibit thrombin (Factor IIa). Heparin also prevents the formation of a stable fibrin clot by inhibiting the activation of the fibrin stabilizing factor. Heparin does not have fibrinolytic activity; therefore, it will not lyse existing clots.

12.2 Pharmacodynamics

Various times (activated clotting time, activated partial thromboplastin time, prothrombin time, whole blood clotting time) are prolonged by full therapeutic doses of heparin; in most cases, they are not measurably affected by low doses of heparin. Bleeding time is usually unaffected by heparin.

12.3 Pharmacokinetics

Absorption

Heparin is not absorbed through the gastrointestinal tract and therefore administered via parenteral route. Peak plasma concentration and the onset of action are achieved immediately after intravenous administration.

Distribution

Heparin is highly bound to antithrombin, fibrinogens, globulins, serum proteases and lipoproteins. The volume of distribution is 0.07 L/kg.

Elimination

Metabolism

Heparin does not undergo enzymatic degradation.

Excretion

Heparin is mainly cleared from the circulation by liver and reticuloendothelial cells mediated uptake into extravascular space. Heparin undergoes biphasic clearance, a) rapid saturable clearance (zero order process due to binding to proteins, endothelial cells and macrophages) and b) slower first order elimination. Low doses of heparin are cleared mostly by a saturable, rapid, zero-order process. Slower first order elimination usually occurs with very high doses of heparin and is dependent on renal function. The plasma half-life is dose-dependent, and it ranges from 0.5 to 2 h.

Specific Populations

Geriatric Patients

Patients over 60 years of age, following similar doses of heparin, may have higher plasma levels of heparin and longer activated partial thromboplastin times (APTTs) compared with patients under 60 years of age [see Use in Specific Populations (8.5)].

Renal and Hepatic Impairment

The rate of clearance of unfractionated heparin may be decreased in patients with renal or hepatic impairment. Patients with renal or hepatic impairment, following similar doses of heparin may have higher plasma levels of heparin compared with patient with normal renal and hepatic function [see Warnings and Precautions (5.2)].

13 NONCLINICAL TOXICOLOGY

13.1 Carcinogenesis, Mutagenesis, Impairment of Fertility

Long term studies in animals to evaluate the carcinogenic potential, reproduction studies in animals to determine effects on fertility of males and females, and the studies to determine mutagenic potential have not been conducted.

16 HOW SUPPLIED/STORAGE AND HANDLING

Heparin Sodium in 5% Dextrose Injection is supplied sterile and nonpyrogenic in single-dose EXCEL® Containers packaged 24 per case.

NDC | REF | Concentration | Size
0264-9567-10 | P5671 | Heparin Sodium 20,000 USP units per 500 mL (40 USP units per mL) in 5% Dextrose Injection | 500 mL
0264-9577-10 | P5771 | Heparin Sodium 25,000 USP units per 500 mL (50 USP units per mL) in 5% Dextrose Injection | 500 mL
0264-9587-20 | P5872 | Heparin Sodium 25,000 USP units per 250 mL (100 USP units per mL) in 5% Dextrose Injection | 250 mL

Exposure of pharmaceutical products to heat should be minimized. Avoid excessive heat. Protect from freezing.

Store at 20°C to 25°C (68°F to 77°F). Excursions permitted to 15°C to 30°C (59°F to 86°F). [See USP Controlled Room Temperature.]

17 PATIENT COUNSELING INFORMATION

Hemorrhage

Inform patients that it may take them longer than usual to stop bleeding, that they may bruise and/or bleed more easily when they are treated with heparin, and that they should report any unusual bleeding or bruising to their physician. Hemorrhage can occur at virtually any site in patients receiving heparin. Fatal hemorrhages have occurred [see Warnings and Precautions (5.2)].

Prior to Surgery

Advise patients to inform physicians and dentists that they are receiving heparin before any surgery is scheduled [see Warnings and Precautions (5.2)].

Heparin-Induced Thrombocytopenia

Inform patients of the risk of heparin-induced thrombocytopenia (HIT). HIT may progress to the development of venous and arterial thromboses, a condition known as heparin-induced thrombocytopenia and thrombosis (HITT). HIT or HITT can occur up to several weeks after the discontinuation of heparin therapy [see Warnings and Precautions (5.3 and 5.4)].

Hypersensitivity

Inform patients that generalized hypersensitivity reactions have been reported. Necrosis of the skin has been reported at the site of subcutaneous injection of heparin [see Warnings and Precautions (5.7), Adverse Reactions (6)].

Other Medications

Because of the risk of hemorrhage, advise patients to inform their physicians and dentists of all medications they are taking, including non-prescription medications, and before starting any new medication [see Drug Interactions (7.2)].

Rx only

EXCEL is a registered trademark of B. Braun Medical Inc.

B. Braun Medical Inc.
Bethlehem, PA 18018-3524 USA
1-800-227-2862

Y36-003-071 LD-239-9

PRINCIPAL DISPLAY PANEL - 500 mL container

NDC 0264-9567-10

HEPARIN SODIUM in

5% Dextrose Injection

20,000 USP units per 500 mL

(40 USP units per mL)

LD-306-5 Y94-003-488

For Intravenous Use Only

Each 100 mL contains: Heparin Sodium USP (porcine intestinal mucosa)
4,000 USP Heparin units; Hydrous Dextrose USP 5 g;
Dibasic Sodium Phosphate•7H2O USP 0.41 g; Citric Acid Anhydrous USP 0.093 g;
Sodium Metabisulfite NF (antioxidant) <0.07 g; Water for Injection USP qs

Electrolytes (mEq/liter): Sodium 38; Phosphate (HPO) 30; Citrate 15

WARNING: CONTAINS SULFITES. Do not admix with other drugs.

Sterile. Single dose container. Discard unused portion.

Store at 20°C to 25°C (68°F to 77°F). Excursions permitted to 15°C to 30°C (59°F to 86°F). [See USP Controlled Room Temperature.] Avoid excessive heat. Protect from freezing. Recommended Dosage: see Prescribing Information. Do not remove overwrap until ready for use.

Not made with natural rubber latex, PVC or DEHP.

EXCEL is a registered trademark of B. Braun Medical Inc.

500 mL EXCEL® CONTAINER

Rx only

REF P5671

B. Braun Medical Inc.
Bethlehem, PA 18018-3524 USA
1-800-227-2862

Prepared in USA. API from Spain.

Y94-003-487 LD-305-5

EXP
LOT

PRINCIPAL DISPLAY PANEL - 500 mL container

NDC 0264-9577-10

HEPARIN SODIUM in

5% Dextrose Injection

25,000 USP units per 500 mL

(50 USP units per mL)

LD-308-7 Y94-003-490

For Intravenous Use Only

Each 100 mL contains: Heparin Sodium USP (porcine intestinal mucosa)
5,000 USP Heparin units; Hydrous Dextrose USP 5 g;
Dibasic Sodium Phosphate•7H2O USP 0.41 g; Citric Acid Anhydrous USP 0.093 g;
Sodium Metabisulfite NF (antioxidant) <0.07 g; Water for Injection USP qs

Electrolytes (mEq/liter): Sodium 38; Phosphate (HPO) 30; Citrate 15

WARNING: CONTAINS SULFITES. Do not admix with other drugs.

Sterile. Single dose container. Discard unused portion.

Store at 20°C to 25°C (68°F to 77°F). Excursions permitted to 15°C to 30°C (59°F to 86°F). [See USP Controlled Room Temperature.] Avoid excessive heat. Protect from freezing. Recommended Dosage: see Prescribing Information. Do not remove overwrap until ready for use.

Not made with natural rubber latex, PVC or DEHP.

EXCEL is a registered trademark of B. Braun Medical Inc.

500 mL EXCEL® CONTAINER

Rx only

REF P5771

B. Braun Medical Inc.
Bethlehem, PA 18018-3524 USA
1-800-227-2862

Prepared in USA. API from Spain.

Y94-003-489 LD-307-6

EXP
LOT

PRINCIPAL DISPLAY PANEL - 250 mL container

NDC 0264-9587-20

HEPARIN SODIUM in

5% Dextrose Injection

25,000 USP units per 250 mL

(100 USP units per mL)

LD-310-8 Y94-003-492

For Intravenous Use Only

Each 100 mL contains: Heparin Sodium USP (porcine intestinal mucosa)
10,000 USP Heparin units; Hydrous Dextrose USP 5 g;
Dibasic Sodium Phosphate•7H2O USP 0.41 g; Citric Acid
Anhydrous USP 0.093 g; Sodium Metabisulfite NF
(antioxidant) <0.07 g; Water for Injection USP qs

Electrolytes (mEq/liter): Sodium 38; Phosphate (HPO) 30; Citrate 15

WARNING: CONTAINS SULFITES. Do not admix with other drugs.

Sterile. Single dose container. Discard unused portion.

Store at 20°C to 25°C (68°F to 77°F). Excursions permitted to 15°C to 30°C (59°F to 86°F). [See USP Controlled Room Temperature.] Avoid excessive heat. Protect from freezing. Recommended Dosage: see Prescribing Information. Do not remove overwrap until ready for use.

Not made with natural rubber latex, PVC or DEHP.

EXCEL is a registered trademark of B. Braun Medical Inc.

250 mL EXCEL® CONTAINER

Rx only

REF P5872

B. Braun Medical Inc.

Bethlehem, PA 18018-3524 USA
1-800-227-2862

Prepared in USA. API from Spain.

Y94-003-491 LD-309-7

EXP
LOT